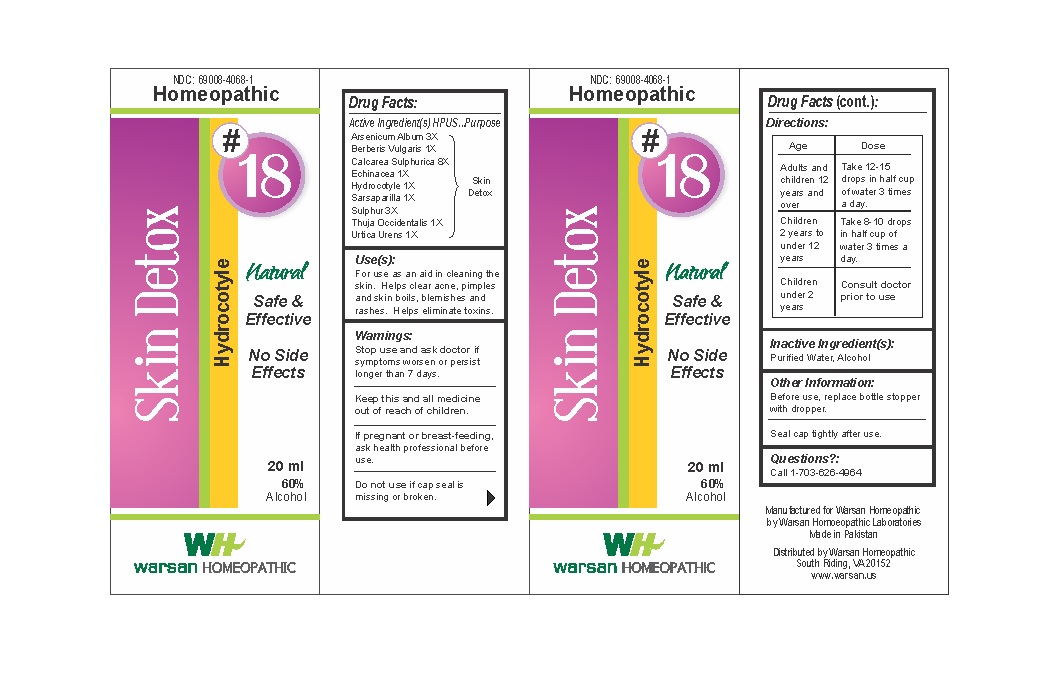 DRUG LABEL: Combination Remedy 18 - Skin Detox
NDC: 69008-4068 | Form: SOLUTION/ DROPS
Manufacturer: Warsan Homoeopathic Laboratories
Category: homeopathic | Type: HUMAN OTC DRUG LABEL
Date: 20171225

ACTIVE INGREDIENTS: ECHINACEA ANGUSTIFOLIA 1 [hp_X]/1 mL; CENTELLA ASIATICA 1 [hp_X]/1 mL; ARSENIC TRIOXIDE 3 [hp_X]/1 mL; SULFUR 3 [hp_X]/1 mL; THUJA OCCIDENTALIS LEAFY TWIG 1 [hp_X]/1 mL; BERBERIS VULGARIS ROOT BARK 1 [hp_X]/1 mL; SARSAPARILLA ROOT 1 [hp_X]/1 mL; URTICA URENS 1 [hp_X]/1 mL
INACTIVE INGREDIENTS: ALCOHOL; WATER

Stop use and ask doctor if symptoms worsen or persist longer than 7 days.

If pregnant or breast-feeding, ask health professional before use.

Do not use if tamper evident seal is missing or broken.

Keep out of reach of children.

ACTIVE INGREDIENT

Arsenicum Album 3X

Berberis Vulgaris 1X

Calcarea Sulphurica 8X

Echinacea 1X

Hydrocotyle 1X

Sarsaparilla 1X

Sulphur 3X

Thuja Occidentalis 1X

Urtica Urens 1X

PURPOSE

For use as an aid in cleaning the skin. Helps clear acne, pimples and skin boils, blemishes and rashes. Helps eliminate toxins.

INACTIVE INGREDIENT

Purified Water

Alcohol

DOSAGE AND ADMINISTRATION

Adults and children 12 years and older: Take 10-15 drops in half cup of water 3 times a day.

Children 2 years to under 12 years: Take 8-10 drops in half cup of water of 3 times a day.

Children under 2 years: Consult doctor prior to use.

INDICATIONS AND USAGE

For use as an aid in cleaning the skin. Helps clear acne, pimples and skin boils, blemishes and rashes. Helps eliminate toxins